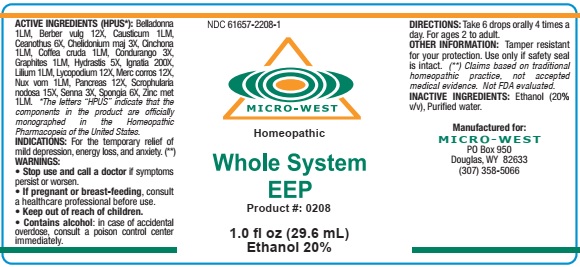 DRUG LABEL: Whole System EEP
NDC: 61657-0208 | Form: LIQUID
Manufacturer: White Manufacturing Inc. DBA Micro-West
Category: homeopathic | Type: HUMAN OTC DRUG LABEL
Date: 20210121

ACTIVE INGREDIENTS: MERCURIC CHLORIDE 12 [hp_X]/30 mL; BERBERIS VULGARIS ROOT BARK 12 [hp_X]/30 mL; LYCOPODIUM CLAVATUM SPORE 12 [hp_X]/30 mL; SUS SCROFA PANCREAS 12 [hp_X]/30 mL; BOS TAURUS PITUITARY GLAND 12 [hp_X]/30 mL; CHELIDONIUM MAJUS 3 [hp_X]/30 mL; MARSDENIA CONDURANGO BARK 3 [hp_X]/30 mL; GOLDENSEAL 3 [hp_X]/30 mL; SENNA LEAF 3 [hp_X]/30 mL; CEANOTHUS AMERICANUS LEAF 6 [hp_X]/30 mL; SPONGIA OFFICINALIS SKELETON, ROASTED 6 [hp_X]/30 mL; SCROPHULARIA NODOSA 15 [hp_X]/30 mL; STRYCHNOS IGNATII SEED 200 [hp_X]/30 mL; ATROPA BELLADONNA 1 [hp_M]/30 mL; ARABICA COFFEE BEAN 1 [hp_M]/30 mL; CAUSTICUM 5 [hp_M]/30 mL; CINCHONA OFFICINALIS BARK 5 [hp_M]/30 mL; LILIUM LANCIFOLIUM WHOLE FLOWERING 5 [hp_M]/30 mL; ZINC 3 [hp_M]/30 mL; GRAPHITE 2 [hp_M]/30 mL; HUMAN BREAST TUMOR CELL 10 [hp_M]/30 mL; HYOSCYAMINE 10 [hp_M]/30 mL; STRYCHNOS NUX-VOMICA SEED 10 [hp_M]/30 mL
INACTIVE INGREDIENTS: ALCOHOL

ACTIVE INGREDIENTS

Belladonna 1M

Berber vulg 12X

Causticum 5M

Ceanothus 6X

Chelidonium maj 3X

Cinchona 5M

Coffea cruda 1M

Condurango 3X

Graphites 2M

Hydrastis 3X

Hysocyaminum 10M

Ignatia 200x

Lillium 5M

Lycopodium 12X

Merc corros 12X

Nux vom 10M

Pancreas suis 12X

Scrophularia nodosa 15X

Senna 3X

Spongia 6X

Zinc met 3M

PURPOSE

For the temporary relief of depresson, energy loss, anxiety

KEEP OUT OF REACH OF CHILDREN

WARNINGS SECTION

WARNINGS: WARNINGS: STOP USE AND CALL A DOCTOR if symptoms persist or worsen. CONTAINS ALCOHOL: in case of accidental overdose, consult a poison control center immediately

OTHER INFORMATION: Tamper resistant for your protection. Use only if safety seal is intact

INDICATIONS

INDICATIONS: For the temporary relief of depresson, energy loss, anxiety

INACTIVE INGREDIENTS

Alcohol 20% v/v

Purified water

DIRECTIONS

DIRECTIONS: Take 6 drops orally, 4 times a day. For ages 2 to adult

MANUFACTURE

MANUFACTURED FOR

MICRO-WEST

P.O. BOX 950

DOUGLAS, WY 82633

1-307-358-5066

LABEL

NDC: 61657-2208-1

MICRO - WEST

Homeopathic

Whole System

EEP

Product #: 0208

1.0 fl oz (29.6 mL)

Ethanol 20%